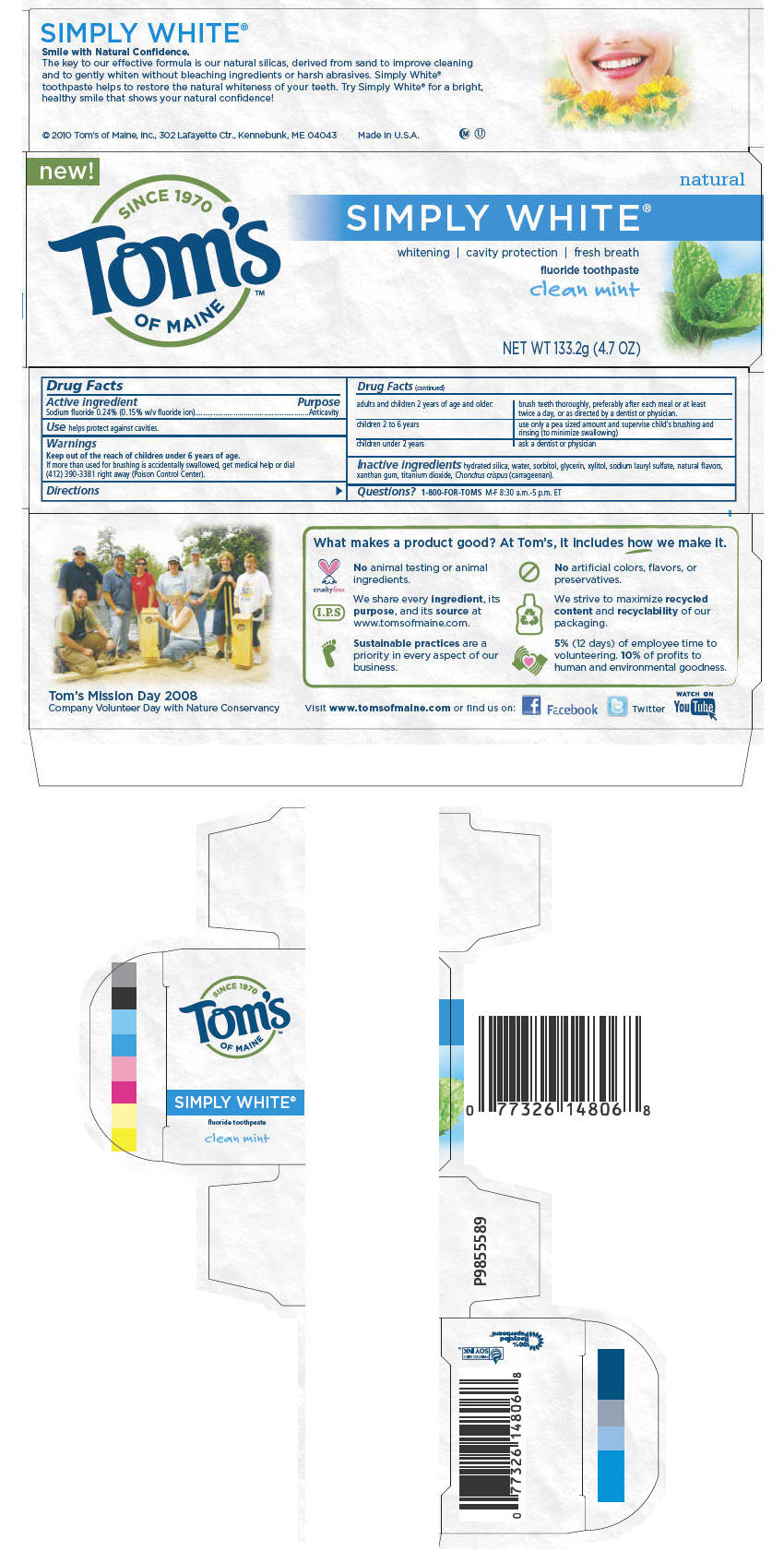 DRUG LABEL: Simply White
NDC: 51009-148 | Form: PASTE, DENTIFRICE
Manufacturer: Tom's of Maine, Inc.
Category: otc | Type: HUMAN OTC DRUG LABEL
Date: 20110203

ACTIVE INGREDIENTS: Sodium fluoride 0.0024 g/1 g
INACTIVE INGREDIENTS: Sorbitol; Water; Silicon Dioxide; Glycerin; Xylitol; Sodium lauryl sulfate; Menthol; Xanthan gum; Peppermint oil; Carrageenan; Spearmint oil; Titanium dioxide

SIMPLY WHITE®

Drug Facts

Active ingredient

Sodium fluoride 0.24% (0.15% w/v fluoride ion)

Purpose

Anticavity

Use

helps protect against cavities.

Warnings

KEEP OUT OF REACH OF CHILDREN

Keep out of the reach of children under 6 years of age.

If more than used for brushing is accidentally swallowed, get medical help or dial (412) 390-3381 right away (Poison Control Center).

Directions

adults and children 2 years of age and older: | brush teeth thoroughly, preferably after each meal or at least twice a day, or as directed by a dentist or physician.
children 2 to 6 years | use only a pea sized amount and supervise child's brushing and rinsing (to minimize swallowing)
children under 2 years | ask a dentist or physician

Inactive ingredients

hydrated silica, water, sorbitol, glycerin, xylitol, sodium lauryl sulfate, natural flavors, xanthan gum, titanium dioxide, Chondrus crispus (carrageenan).

Questions?

1-800-FOR-TOMS M-F 8:30 a.m.-5 p.m. ET

© 2010 Tom's of Maine, Inc., 302 Lafayette Ctr., Kennebunk, ME 04043
Made in U.S.A.

PRINCIPAL DISPLAY PANEL - 133.2g Tube Carton

new!

SINCE 1970
Tom's
OF MAINE™

natural

SIMPLY WHITE®
whitening | cavity protection | fresh breath
fluoride toothpaste
clean mint

NET WT 133.2g (4.7 OZ)